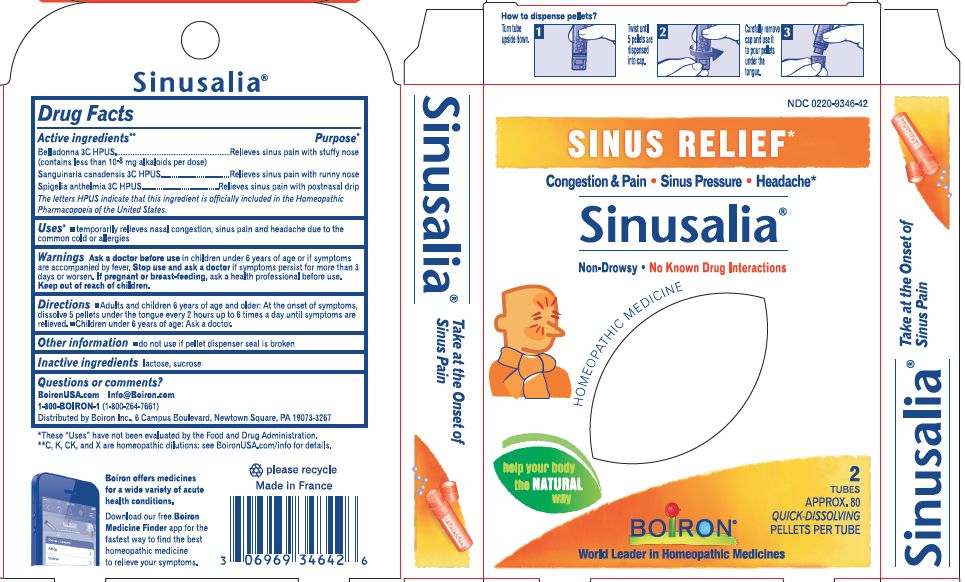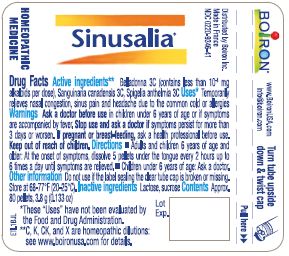 DRUG LABEL: Sinusalia
NDC: 0220-9346 | Form: PELLET
Manufacturer: Laboratoires Boiron
Category: homeopathic | Type: HUMAN OTC DRUG LABEL
Date: 20201102

ACTIVE INGREDIENTS: ATROPA BELLADONNA 3 [hp_C]/1 1; SANGUINARIA CANADENSIS ROOT 3 [hp_C]/1 1; SPIGELIA ANTHELMIA 3 [hp_C]/1 1
INACTIVE INGREDIENTS: SUCROSE; LACTOSE

Sinusalia Pellets

ACTIVE INGREDIENT

Belladonna 3C, Sanguinaria canadensis 3C, Spigelia anthelmia 3C

INDICATIONS AND USAGE

Temporary relieves nasal congestion, sinus pain and headache, due to common cold or allergies.

Do not use if pellet dispenser seal is broken

DOSAGE AND ADMINISTRATION

Adults and children 6 years of age and older: Dissolve 5 pellets in the mouth every 2 hours up to 6 times a day until symptoms are relieved.

INACTIVE INGREDIENT

lactose, sucrose.

HOW SUPPLIED

Approx. 80 pellets, 3.8 g (0.133 oz.).

PURPOSE

Belladonna 3C..... Relieves sinus pain with stuffy nose
Sanguinaria canadensis 3C ..... Relieves sinus pain with runny nose
Spigelia anthelmia 3C ..... Relieves sinus pain with postnasal drip.

Questions, Comments?
www.boironusa.com

Info@boiron.com

1-800-BOIRON-1
(1-800-264-7661)

Distributed by Boiron Inc.
6 campus boulevard
Newtown Square, PA 19073-3267

Ask a doctor before use in children younger than 6 years of age or if symptoms are accompanied by fever.

Stop use and ask doctor if symptoms persist for more than 3 days or worsen.

Keep out of reach of children.